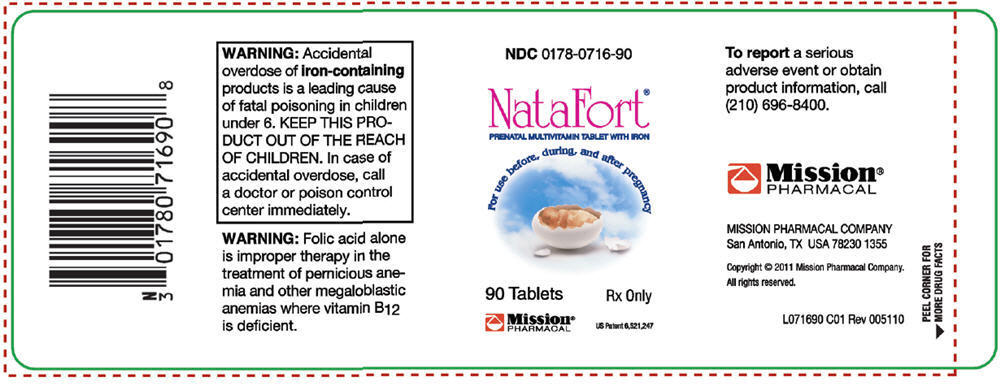 DRUG LABEL: NataFort
NDC: 0178-0716 | Form: TABLET
Manufacturer: Mission Pharmacal Company
Category: prescription | Type: HUMAN PRESCRIPTION DRUG LABEL
Date: 20110810

ACTIVE INGREDIENTS: Ascorbic acid 120 mg/1 1; Cholecalciferol 400 [iU]/1 1; .alpha.-tocopherol acetate, dl- 11 [iU]/1 1; Thiamine mononitrate 2 mg/1 1; Riboflavin 3 mg/1 1; Niacinamide 20 mg/1 1; Pyridoxine Hydrochloride 10 mg/1 1; Folic Acid 1 mg/1 1; Cyanocobalamin 12 ug/1 1; Iron 60 mg/1 1
INACTIVE INGREDIENTS: polyethylene glycols; calcium carbonate; povidone; cellulose, microcrystalline; croscarmellose sodium; titanium dioxide; magnesium silicate; vitamin a palmitate; magnesium stearate; ethyl vanillin; Dimethylaminoethyl methacrylate - butyl methacrylate - methyl methacrylate copolymer

NataFort®
PRENATAL MULTIVITAMIN TABLET WITH IRON

DESCRIPTION

NataFort® is a prescription prenatal/postnatal multivitamin/mineral supplement. The tablet is white, coated, and oval in shape, and is debossed "N1" on one side and is blank on the other.

Each prenatal tablet contains:
Vitamin C (Ascorbic acid) | 120 mg
Vitamin D3 (Cholecalciferol) | 400 IU
Vitamin E (dl-alpha tocoperyl acetate) | 11 IU
Thiamin (Vitamin B1) | 2 mg
Riboflavin (Vitamin B2) | 3 mg
Niacinamide (Vitamin B3) | 20 mg
Vitamin B6 (Pyridoxine HCl) | 10 mg
Folic Acid | 1 mg
Vitamin B12 (Cyanocobalamin) | 12 mcg
Iron (Ferrous fumarate, carbonyl iron) | 60 mg

INDICATIONS

NataFort® is a multivitamin/mineral prescription drug indicated for use in improving the nutritional status of women prior to conception, throughout pregnancy, and in the postnatal period for both lactating and nonlactating mothers.

CONTRAINDICATIONS

This product is contraindicated in patients with a known hypersensitivity to any of the ingredients.

WARNING

Accidental overdose of iron-containing products is a leading cause of fatal poisoning in children under 6. KEEP THIS PRODUCT OUT OF THE REACH OF CHILDREN. In case of accidental overdose, call a doctor or poison control center immediately.

WARNING

Folic acid alone is improper therapy in the treatment of pernicious anemia and other megaloblastic anemias where vitamin B12 is deficient.

PRECAUTIONS

Folic acid in doses above 0.1 mg daily may obscure pernicious anemia in that hematologic remission can occur while neurological manifestations progress.

ADVERSE REACTIONS

Allergic sensitization has been reported following both oral and parenteral administration of folic acid.

DOSAGE AND ADMINISTRATION

One tablet daily or as directed by a physician.

STORAGE AND HANDLING

Store at controlled room temperature.

NOTICE: Contact with moisture can discolor or erode the tablet.

HOW SUPPLIED

Bottles of 90 tablets each - NDC 0178-0716-90.

US Patent 6,521,247

MISSION PHARMACAL COMPANY
San Antonio, TX USA 78230 1355

Copyright © 2011 Mission Pharmacal Company.

All rights reserved.

L071690 C01 Rev 005110

PRINCIPAL DISPLAY PANEL - 90 Tablet Bottle Label

NDC 0178-0716-90

NataFort®
PRENATAL MULTIVITAMIN TABLET WITH IRON
For use before, during and after pregnancy

90 Tablets

Rx Only

Mission®
PHARMACAL

US Patent 6,521,247